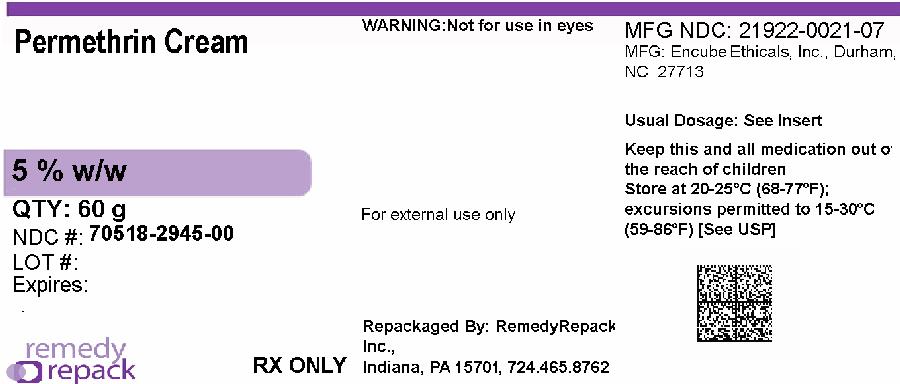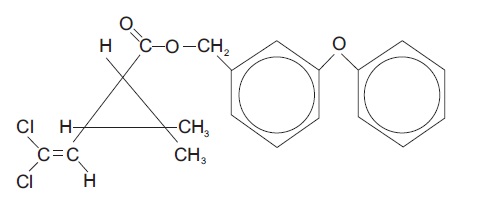 DRUG LABEL: Permethrin
NDC: 70518-2945 | Form: CREAM
Manufacturer: REMEDYREPACK INC.
Category: prescription | Type: HUMAN PRESCRIPTION DRUG LABEL
Date: 20260213

ACTIVE INGREDIENTS: PERMETHRIN 50 mg/1 g
INACTIVE INGREDIENTS: CARBOMER HOMOPOLYMER TYPE B (ALLYL PENTAERYTHRITOL CROSSLINKED); MEDIUM-CHAIN TRIGLYCERIDES; GLYCERIN; GLYCERYL MONO AND DIPALMITOSTEARATE; ISOPROPYL MYRISTATE; LANOLIN ALCOHOLS; MINERAL OIL; CETETH-20; SODIUM HYDROXIDE; FORMALDEHYDE; WATER

PERMETHRIN CREAM 5% W/W
Rx Only

DESCRIPTION

Permethrin Cream 5% w/w is a topical scabicidal agent for the treatment of infestation with Sarcoptesscabiei(scabies). It is available in an off-white, vanishing cream base. Permethrin Cream 5% w/w is for topical use only.

Chemical Name- The permethrin used is an approximate 1:3 mixture of the cis and trans isomers of the pyrethroid 3-(2,2-dichloroethenyl)-2,2- dimethylcyclopropanecarboxylic acid, (3-phenoxyphenyl) methyl ester. Permethrin has a molecular formula of C21H20Cl2O3and a molecular weight of 391.29. It is a yellow to light orange-brown, low melting solid or viscous liquid.
Active Ingredient- Each gram contains permethrin 50 mg (5%).
Inactive Ingredients - Carbomer homopolymer type B, medium-chain triglycerides, glycerin, mono-and diglycerides, isopropyl myristate, lanolin alcohols, mineral oil, polyoxyethylene (20) cetyl ethers, purified water, and sodium hydroxide. Formaldehyde 1 mg (0.1%) is added as a preservative.

CLINICAL PHARMACOLOGY

Permethrin, a pyrethroid, is active against a broad range of pests including lice, ticks, fleas, mites, and other arthropods. It acts on the nerve cell membrane to disrupt the sodium channel current by which the polarization of the membrane is regulated. Delayed repolarization and paralysis of the pests are the consequences of this disturbance.
Permethrin is rapidly metabolized by ester hydrolysis to inactive metabolites which are excreted primarily in the urine. Although the amount of permethrin absorbed after a single application of the 5% cream has not been determined precisely, data from studies with^14C-labeled permethrin and absorption studies of the cream applied to patients with moderate to severe scabies indicate it is 2% or less of the amount applied.

INDICATIONS AND USAGE

Permethrin Cream 5% w/w is indicated for the treatment of infestation with Sarcoptesscabiei (scabies).

CONTRAINDICATIONS

Permethrin Cream 5% w/w is contraindicated in patients with known hypersensitivity to any of its components, to any synthetic pyrethroid or pyrethrin.

WARNINGS

If hypersensitivity to Permethrin Cream 5% w/w occurs, discontinue use.

PRECAUTIONS

General

Scabies infestation is often accompanied by pruritus, edema, and erythema. Treatment with Permethrin Cream 5% w/w may temporarily exacerbate these conditions.

Information for Patients

Patients with scabies should be advised that itching, mild burning and/or stinging may occur after application of Permethrin Cream 5% w/w. In clinical trials, approximately 75% of patients treated with Permethrin Cream 5% w/w who continued to manifest pruritus at 2 weeks had cessation by 4 weeks. If irritation persists, they should consult their physician. Permethrin Cream 5% w/w may be very mildly irritating to the eyes. Patients should be advised to avoid contact with eyes during application and to flush with water immediately if Permethrin Cream 5% w/w gets in the eyes.

Repackaged By / Distributed By: RemedyRepack Inc.

625 Kolter Drive, Indiana, PA 15701

(724) 465-8762

Carcinogenesis, Mutagenesis, Impairment of Fertility

Six carcinogenicity bioassays were evaluated with permethrin, three each in rats and mice. No tumorigenicity was seen in the rat studies. However, species-specific increases in pulmonary adenomas, a common benign tumor of mice of high spontaneous background incidence, were seen in the three mouse studies. In one of these studies there was an increased incidence of pulmonary alveolar-cell carcinomas and benign liver adenomas only in female mice when permethrin was given in their food at a concentration of 5000 ppm. Mutagenicity assays, which give useful correlative data for interpreting results from carcinogenicity bioassays in rodents, were negative. Permethrin showed no evidence of mutagenic potential in a battery of in vitro and in vivo genetic toxicity studies. Permethrin did not have any adverse effect on reproductive function at a dose of 180 mg/kg/day orally in a three-generation rat study.

Pregnancy: Teratogenic Effects: Pregnancy Category B

Reproduction studies have been performed in mice, rats, and rabbits (200 to 400 mg/kg/day orally) and have revealed no evidence of impaired fertility or harm to the fetus due to permethrin. There are, however, no adequate and well-controlled studies in pregnant women. Because animal reproduction studies are not always predictive of human response, this drug should be used during pregnancy only if clearly needed.

Nursing Mothers

It is not known whether this drug is excreted in human milk. Because many drugs are excreted in human milk and because of the evidence for tumorigenic potential of permethrin in animal studies, consideration should be given to discontinuing nursing temporarily or withholding the drug while the mother is nursing.

Pediatric Use

Permethrin Cream 5% w/w is safe and effective in pediatric patients two months of age and older. Safety and effectiveness in infants less than two months of age have not been established.

Geriatric Use

Clinical studies of Permethrin Cream 5% w/w did not identify sufficient numbers of subjects aged 65 and over to allow a definitive statement regarding whether elderly subjects respond differently from younger subjects. Other reported clinical experience has not identified differences in responses between the elderly and younger patients. This drug is known to be substantially excreted by the kidney. However, since topical permethrin is metabolized in the liver and excreted in the urine as inactive metabolites, there does not appear to be an increased risk of toxic reactions in patients with impaired renal function when used as labeled.

ADVERSE REACTIONS

In clinical trials, generally mild and transient burning and stinging followed application with Permethrin Cream 5% w/w in 10% of patients and was associated with the severity of infestation. Pruritus was reported in 7% of patients at various times post-application. Erythema, numbness, tingling, and rash were reported in 1 to 2% or less of patients (see PRECAUTIONS - General). Other adverse events reported since marketing Permethrin Cream 5% w/w include: headache, fever, dizziness, abdominal pain, diarrhea and nausea and/or vomiting. Although extremely uncommon and not expected when used as directed (see DOSAGE AND ADMINISTRATION), rare occurrences of seizure have been reported. None have been medically confirmed as associated with Permethrin Cream 5% w/w treatment.

OVERDOSAGE

No instance of accidental ingestion of Permethrin Cream 5% w/w has been reported. If ingested, gastric lavage and general supportive measures should be employed. Excessive topical use (see DOSAGE AND ADMINISTRATION) may result in increased irritation and erythema.

DOSAGE AND ADMINISTRATION

Adults and children- Thoroughly massage Permethrin Cream 5% w/w into the skin from the head to the soles of the feet. Scabies rarely infests the scalp of adults, although the hairline, neck, temple, and forehead may be infested in infants and geriatric patients. Usually 30 grams is sufficient for an average adult. The cream should be removed by washing (shower or bath) after 8 to 14 hours. Infants should be treated on the scalp, temple, and forehead. ONE APPLICATION IS GENERALLY CURATIVE.
Patients may experience persistent pruritus after treatment. This is rarely a sign of treatment failure and is not an indication for retreatment. Demonstrable living mites after 14 days indicate that retreatment is necessary.

HOW SUPPLIED

Permethrin Cream 5% w/w is available as follows:

NDC: 70518-2945-00

PACKAGING: 1 in 1 CARTON, 60 g in 1 TUBE TYPE 0

STORAGE

Store at 20-25°C (68-77°F) [see USP Controlled Room Temperature].

Repackaged and Distributed By:

Remedy Repack, Inc.

625 Kolter Dr. Suite #4 Indiana, PA 1-724-465-8762

PACKAGE LABEL

DRUG: Permethrin

GENERIC: Permethrin Cream 5% w/w

DOSAGE: CREAM

ADMINSTRATION: TOPICAL

NDC: 70518-2945-0

PACKAGING: 60 g in 1 TUBE

OUTER PACKAGING: 1 in 1 CARTON

ACTIVE INGREDIENT(S):

- PERMETHRIN 50mg in 1g

INACTIVE INGREDIENT(S):

- CARBOMER HOMOPOLYMER TYPE B (ALLYL PENTAERYTHRITOL CROSSLINKED)
- MEDIUM-CHAIN TRIGLYCERIDES
- GLYCERIN
- GLYCERYL MONO AND DIPALMITOSTEARATE
- ISOPROPYL MYRISTATE
- LANOLIN ALCOHOLS
- MINERAL OIL
- CETETH-20
- SODIUM HYDROXIDE
- FORMALDEHYDE
- WATER